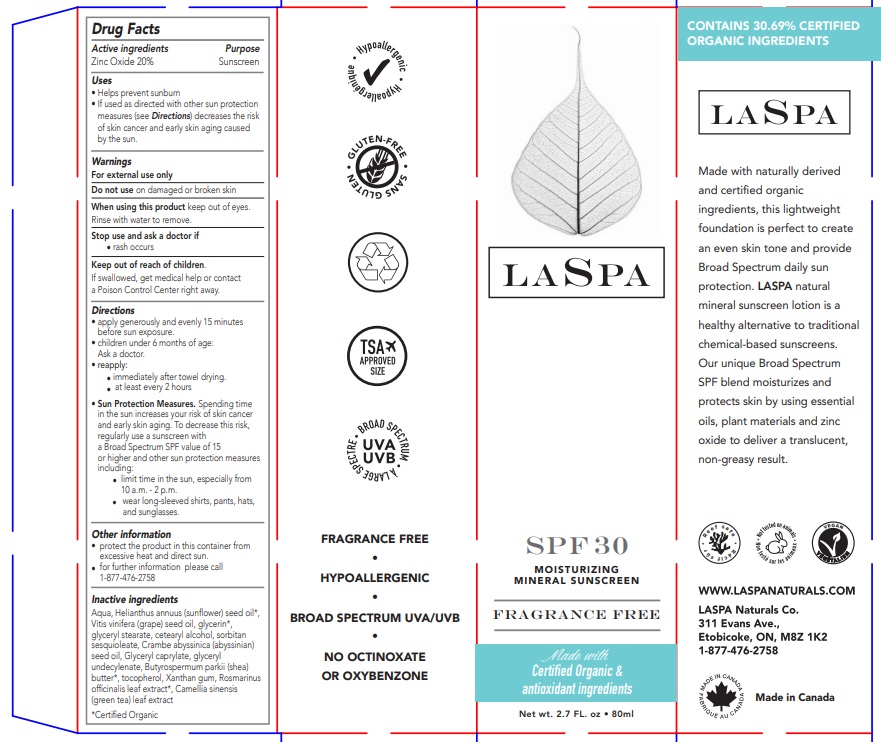 DRUG LABEL: LaSpa Moisturizing Mineral Sunscreen SPF 30
NDC: 71780-021 | Form: CREAM
Manufacturer: The Green Cricket inc
Category: otc | Type: HUMAN OTC DRUG LABEL
Date: 20211013

ACTIVE INGREDIENTS: ZINC OXIDE 200 mg/1 mL
INACTIVE INGREDIENTS: GLYCERYL 1-UNDECYLENATE; SHEA BUTTER; CETOSTEARYL ALCOHOL; WATER; SUNFLOWER OIL; GRAPE SEED OIL; SORBITAN SESQUIOLEATE; TOCOPHEROL; GLYCERIN; GLYCERYL MONOSTEARATE; XANTHAN GUM; ROSEMARY; CRAMBE HISPANICA SUBSP. ABYSSINICA SEED OIL; GLYCERYL CAPRYLATE; GREEN TEA LEAF

LASPA MOISTURIZING MINERAL SUNSCREEN

Active ingredients

Zinc Oxide 20%

Uses

- Helps prevent sunburn
- If used as directed with other sun protection measures (see Directions) decreases the risk of skin cancer and early skin aging caused by the sun.

Purpose

Sunscreen

Warnings

For external use only

Do not use on damaged or broken skin

When using this product keep out of eyes. Rinse with water to remove.

Stop use and ask a doctor if rash occurs

Keep out of reach of children

If swallowed, get medical help or contact a Poison Control Center right away.

Directions

- apply generously and evenly 15 minutes before sun exposure.
- children under 6 months of age: Ask a doctor.
- reapply:
  - immediately after towel drying.
  - at least every 2 hours
  - Sun Protection Measures. Spending time in the sun increases your risk of skin cancer and early skin aging. To decrease this risk, regularly use a sunscreen with a Broad Spectrum SPF value of 15 or higher and other sun protection measures including:
  - limit time in the sun, especially from 10 a.m. - 2 p.m.
  - wear long-sleeved shirts, pants, hats, and sunglasses.

Other information

- protect the product in this container from excessive heat and direct sun.
- for further information please call 1-877-476-2758

Inactive ingredients

Aqua, Helianthus annuus (sunflower) seed oil*, Vitis vinifera (grape) seed oil, glycerin*, glyceryl stearate, cetearyl alcohol, sorbitan sesquioleate, Crambe abyssinica (abyssinian) seed oil, Glyceryl caprylate, glyceryl undecylenate, Butyrospermum parkii (shea) butter*, tocopherol, Xanthan gum, Rosmarinus officinalis leaf extract*, Camellia sinensis (green tea) leaf extract *Certified Organic